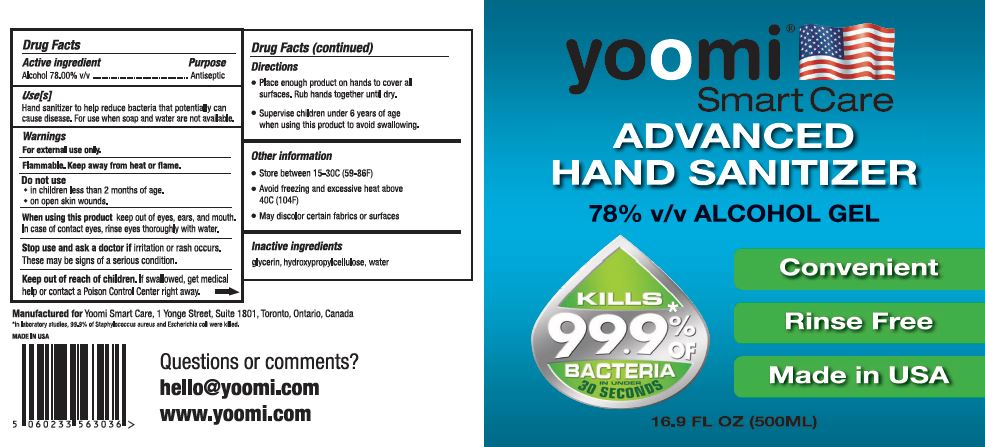 DRUG LABEL: Hand Sanitizer
NDC: 72686-180 | Form: GEL
Manufacturer: Fareva Morton Grove, Inc.
Category: otc | Type: HUMAN OTC DRUG LABEL
Date: 20201029

ACTIVE INGREDIENTS: ALCOHOL 78 mL/100 mL
INACTIVE INGREDIENTS: HYDROXYPROPYL CELLULOSE, UNSPECIFIED 1.28 mL/100 mL; WATER; GLYCERIN 1.72 mL/100 mL

1. Alcohol (ethanol) (USP or Food Chemical Codex (FCC) grade) (78%, volume/volume (v/v)) in an aqueous solution denatured according to Alcohol and Tobacco Tax and Trade Bureau regulations in 27 CFR part 20.
2. Glycerin (1.72% v/v).
3. Hydroxypropylcellulose (1.28% v/v).
4. Sterile distilled water or boiled cold water.

Active Ingredient(s)

Alcohol 78% v/v. Purpose: Antiseptic

Purpose

Antiseptic, Hand Sanitizer

Use

Hand Sanitizer to help reduce bacteria that potentially can cause disease. For use when soap and water are not available.

Warnings

For external use only. Flammable. Keep away from heat or flame

Do not use

- in children less than 2 months of age
- on open skin wounds

When using this product keep out of eyes, ears, and mouth. If contact with eyes, rinse eyes thoroughly with water.

Stop use and ask a doctor if irritation or rash occurs. These may be signs of a serious condition.

Keep out of reach of children. If swallowed, get medical help or contact a Poison Control Center right away.

Directions

- Place enough product on hands to cover all surfaces. Rub hands together until dry.
- Supervise children under 6 years of age when using this product to avoid swallowing.

Other information

- Store between 15-30C (59-86F)
- Avoid freezing and excessive heat above 40C (104F)
  - May discolor certain fabrics or surfaces

Inactive ingredients

glycerin, hydroxypropylcellulose, water

Package Label - Principal Display Panel

500 mL NDC: 72686-180-14

Yoomi 16-9 label.jpg